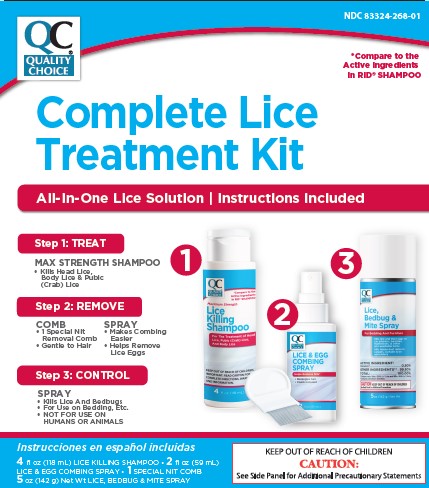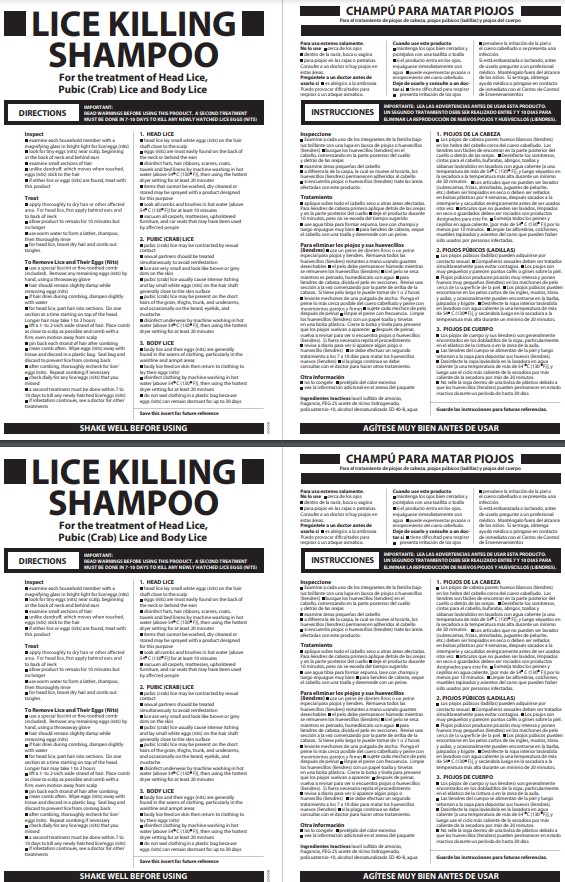 DRUG LABEL: Quality Choice Lice Treatment
NDC: 83324-268 | Form: KIT | Route: TOPICAL
Manufacturer: Chain Drug Marketing Association
Category: otc | Type: HUMAN OTC DRUG LABEL
Date: 20251112

ACTIVE INGREDIENTS: PIPERONYL BUTOXIDE 40 mg/1 mL; PYRETHRUM EXTRACT 3.3 mg/1 mL
INACTIVE INGREDIENTS: POLYQUATERNIUM-10 (400 MPA.S AT 2%); AMMONIUM LAURETH-2 SULFATE; ALCOHOL; WATER; PEG-25 HYDROGENATED CASTOR OIL

Quality Choice Lice treatment Kit

ACTIVE INGREDIENT

Piperonyl butoxide 4%

Pyrethrum extract (equivalent to 0.33% pyrethrins)

INDICATIONS AND USAGE

treats head, pubic (crab), and body lice

PURPOSE

Lice treatment

WARNINGS

For external use only

DO NOT USE

- near eyes
- inside nose, mouth, or vagina
- on lice in eyebrows or eyelashes. See a doctor if lice are present in these areas.

ASK DOCTOR

- allergic to ragweed. May cause breathing difficulty or an asthmatic attack.

WHEN USING

- keep eyes tightly closed and protect eyes with a washcloth or towel
- if product gets into eyes, flush with water right away
- scalp itching or redness may occur

STOP USE

- breathing difficulty occurs
- eye irritation occurs
- skin or scalp irritation continues or infection occurs

KEEP OUT OF REACH OF CHILDREN

If swallowed, get medical help or contact a Poison Control Center right away.

DOSAGE AND ADMINISTRATION

- Important: Read warnings before use
- Adults and children 2 years and over:

Inspect

- check each household member with a magnifying glass in bright light for lice/nits (eggs)
- look for tiny nits near scalp, beginning at back of neck and behind ears
- examine small sections of hair at a time
- unlike dandruff which moves when touched, nits stick to the hair
- if either lice or nits are found, treat with this product

Treat

- apply thoroughly to DRY HAIR or other affected area. For head lice, first apply behind ears and to back of neck.
- allow product to remain for 10 minutes, but no longer
- use warm water to form a lather, shampoo, then thoroughly rinse
- for head lice, towel dry hair and comb out tangles

Remove lice and their eggs (nits)

- use a fine-tooth or special lice/nit comb. Remove any remaining nits by hand (using a throw-away glove).
- hair should remain slightly damp while removing nits
- if hair dries during combing, dampen slightly with water
- for head lice, part hair into sections. Do one section at a time starting on top of the head. Longer hair may take 1 to 2 hours.
- lift a 1-to 2-inch wide strand of hair. Place comb as close to scalp as possible and comb with a firm, even motion away from scalp.
- pin back each strand of hair after combing
- clean comb often. Wipe nits away with tissue and discard in a plastic bag. Seal bag and discard to prevent lice from coming back.
- after combing, thoroughly recheck for lice/nits. Repeat combing if necessary.
- check daily for any lice/nits that you missed
- a second treatment must be done in 7 to 10 days to kill any newly hatched lice
- if infestation continues, see a doctor for other treatments
- Children under 2 years: ask a doctor

STORAGE AND HANDLING

- do not freeze
- store at controlled room temperature 20°-25°C (68°-77°F)
- see package insert for additional information

Inactive ingredients

ammonium laureth sulfate, fragrance, PEG-25 hydrogenated castor oil, polyquaternium-10, purified water, SD-40 alcohol

PACKAGE LABEL

Quality Choice

The all in one lice solution for your family

Compare to the Active Ingredients in RID® Shampoo†

with maximum strength Shampoo

1 treat shampoo

2 remove comb/gel

3 control spray

Instrucciones en español incluidas